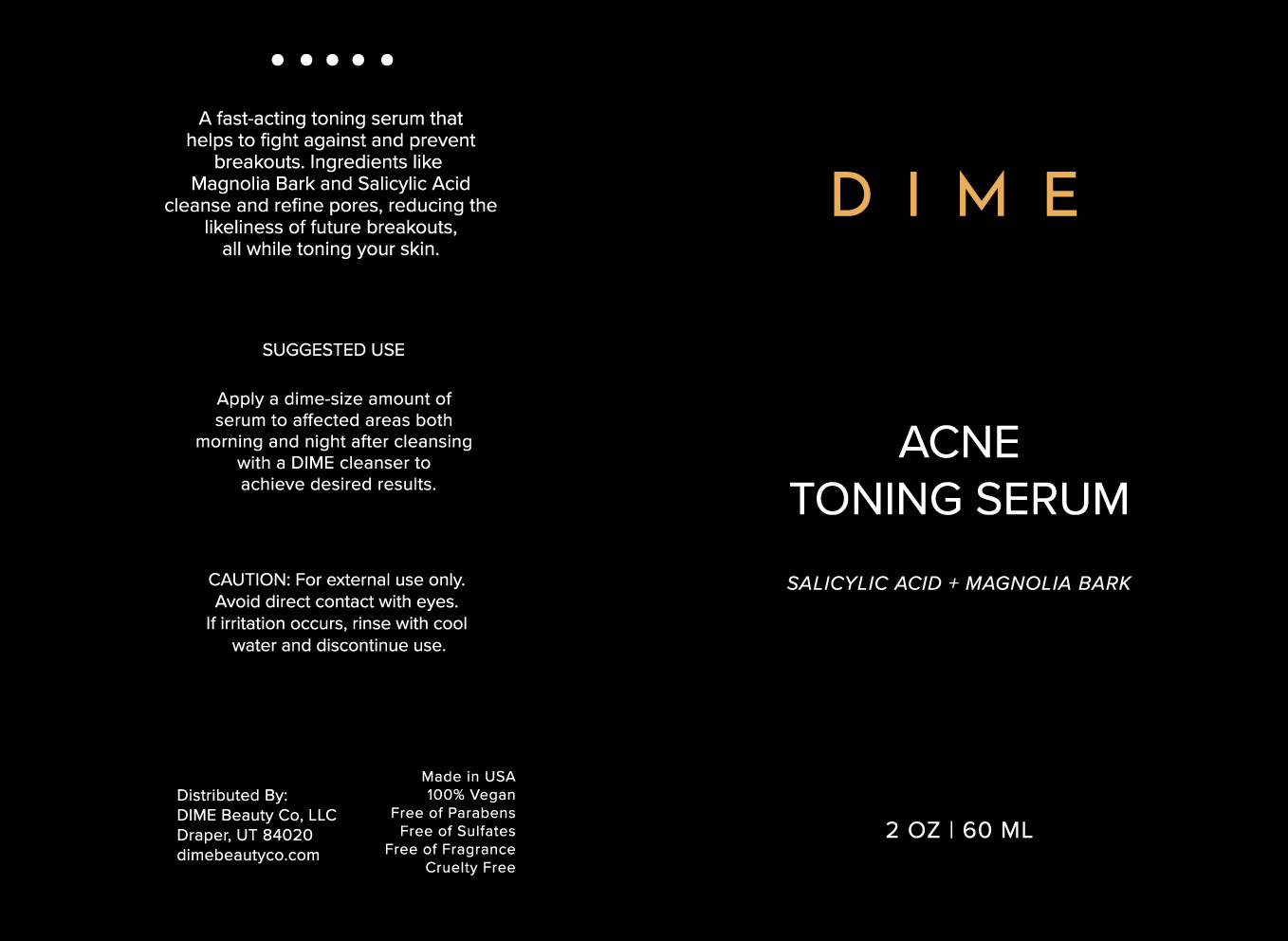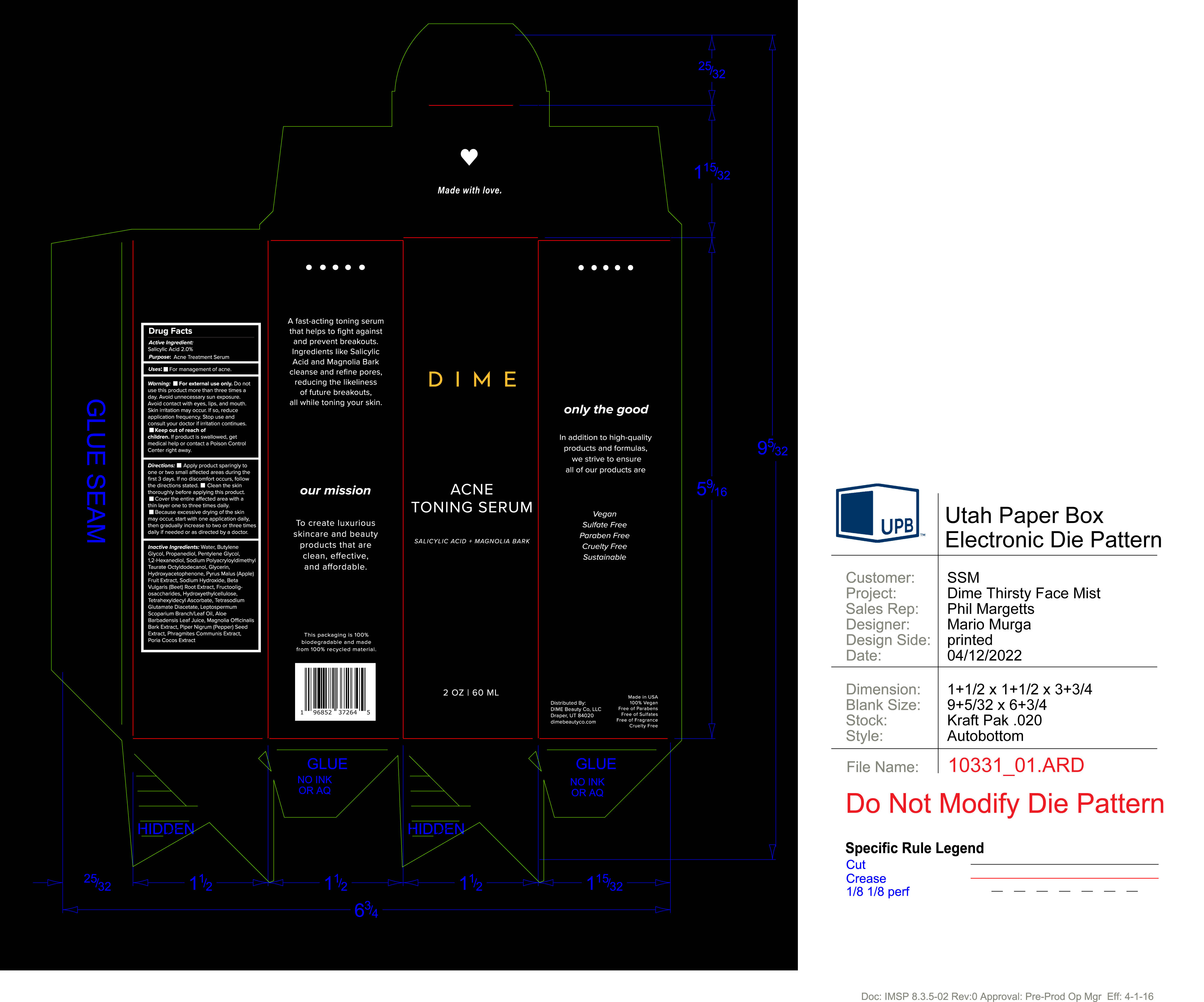 DRUG LABEL: Acne Toner Serum
NDC: 82870-003 | Form: CREAM
Manufacturer: Dime Beauty Co, LLC
Category: otc | Type: HUMAN OTC DRUG LABEL
Date: 20251001

ACTIVE INGREDIENTS: SALICYLIC ACID 2 g/100 mL
INACTIVE INGREDIENTS: 1,2-HEXANEDIOL; PENTYLENE GLYCOL; GLYCERIN; APPLE; TETRAHEXYLDECYL ASCORBATE; PROPANEDIOL; BEET; WHITE PEPPER; WATER; FU LING; TETRASODIUM GLUTAMATE DIACETATE; MANUKA OIL; ALOE VERA LEAF; HYDROXYACETOPHENONE; BUTYLENE GLYCOL; MAGNOLIA OFFICINALIS BARK; SODIUM HYDROXIDE

Acne Toning Serum

Active ingredients:

Salicylic Acid 2.0%

Purpose: Acne Treatment Serum

PURPOSE

Uses: For management of acne

Keep out of reach of children. If product is swallowed, get medical help or contact a Poison Control Center right away.

Stop use and consult a doctor if irritation continues.

Warning:

- For external use only. Do not use this product more than three times a day. Avoid unnecesary sun exposure. Avoid contact with eyes, lip and mouth. Skin irritation may occur. If so, reduce application frequency.

Directions:

- Apply product sparingly to one or two small affected areas during the first 3 days. If no discomfort occurs, follow the directions stated.
- Clean the skin thoroughly before applying this product.
- Cover the entire affected area with a thin layer one to three times daily..
- Because excessive drying of the skin may occur, start with one application daily, then gradually increase to two or three times daily if needed or as directed.

INACTIVE INGREDIENT

Inactive Ingredients: Water, Butylene Glycol, Propanediol, Pentylene Glycol, 1,2-Hexanediol, Sodium Polyacryloyldimethyl Taurate Octyldodecanol, Glycerin, Hydroxyacetophenone, Pyrus Malus (Apple) Fruit Extract, Sodium Hydroxide, Beta Vulgaris (Beet) Root Extract, Fructooligosaccharides, Hydroxyethylcellulose, Tetrahexyldecyl Ascorbate, Tetrasodium Glutamate Diacetate, Leptospermum Scoparium Branch/Leaf Oil, Aloe Barbadensis Leaf Juice, Magnolia Officinalis Bark Extract, Piper Nigrum (Pepper) Seed Extract, Phragmites Communis Extract, Poria Cocos Extract

PACKAGE LABEL

DIME

ACNE TONING SERUM

SALICYLIC ACID + MAGNOLIA BARK

2 OZ 60 ML